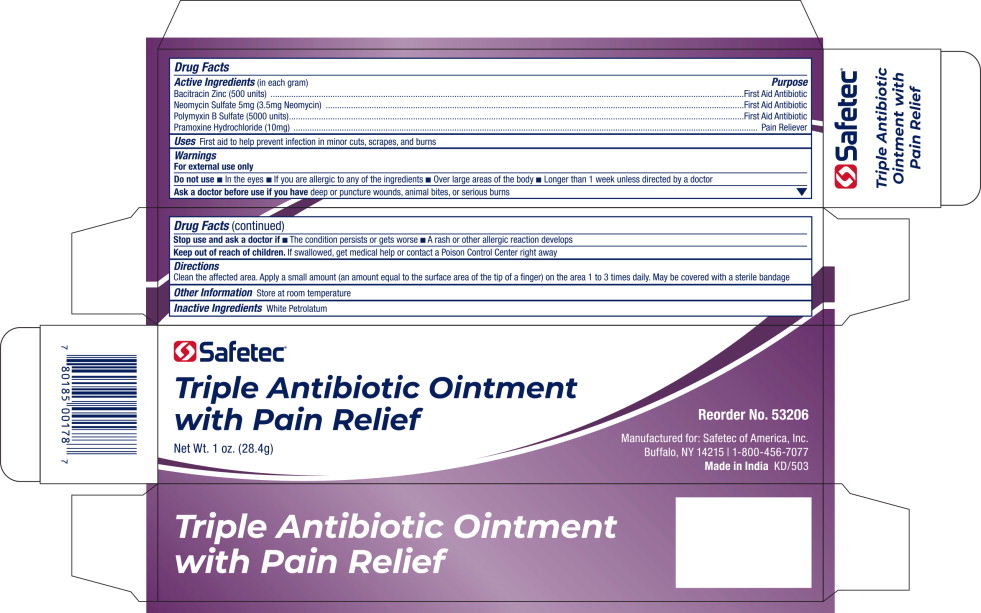 DRUG LABEL: Triple Antibiotic with Pain Relief
NDC: 61010-4401 | Form: OINTMENT
Manufacturer: Safetec of America, Inc.
Category: otc | Type: HUMAN OTC DRUG LABEL
Date: 20240216

ACTIVE INGREDIENTS: BACITRACIN ZINC 500 [iU]/1 g; NEOMYCIN SULFATE 5 mg/1 g; POLYMYXIN B SULFATE 5000 [iU]/1 g; PRAMOXINE HYDROCHLORIDE 10 mg/1 g
INACTIVE INGREDIENTS: PETROLATUM

61010-4401-1, Triple Antibiotic with Pain relief

Drug Facts

Active Ingredients (in each gram)

Bacitracin Zinc (500 units)

Neomycin Sulfate 5mg (3.5mg Neomycin)

Polymyxin B Sulfate (5000 units)

Pramoxine Hydrochloride (10mg)

Purpose

First Aid Antibiotic

First Aid Antibiotic

First Aid Antibiotic

Pain Reliever

Uses

First aid to help prevent infection in minor cuts, scrapes, and burns

Warnings

For external use only

Do not use

- In the eyes
- If you are allergic to any of the ingredients
- Over large areas of the body
- Longer than 1 week unless directed by a doctor

Ask a doctor before use if you havedeep or puncture wounds, animal bites, or serious burns

Stop use and ask a doctor if

- The condition persists or gets worse
- A rash or other allergic reaction develops

Keep out of reach of children.If swallowed, get medical help or contact a Poison Control Center right away

Directions

Clean the affected area. Apply a small amount (an amount equal to the surface area of the tip of a finger) on the area 1 to 3 times daily. May be covered with a sterile bandage

Other Information

Store at room temperature

Inactive Ingredients

White Petrolatum

Principal Display Panel - 1 oz. Tube Label

Safetec®

Triple Antibiotic Ointment
with Pain Relief

Net Wt. 1 oz. (28.4g)

Reorder No. 53206

Manufactured for: Safetec of America, Inc.
Buffalo, NY 14215 | 1-800-456-7077

Made in IndiaKD/503